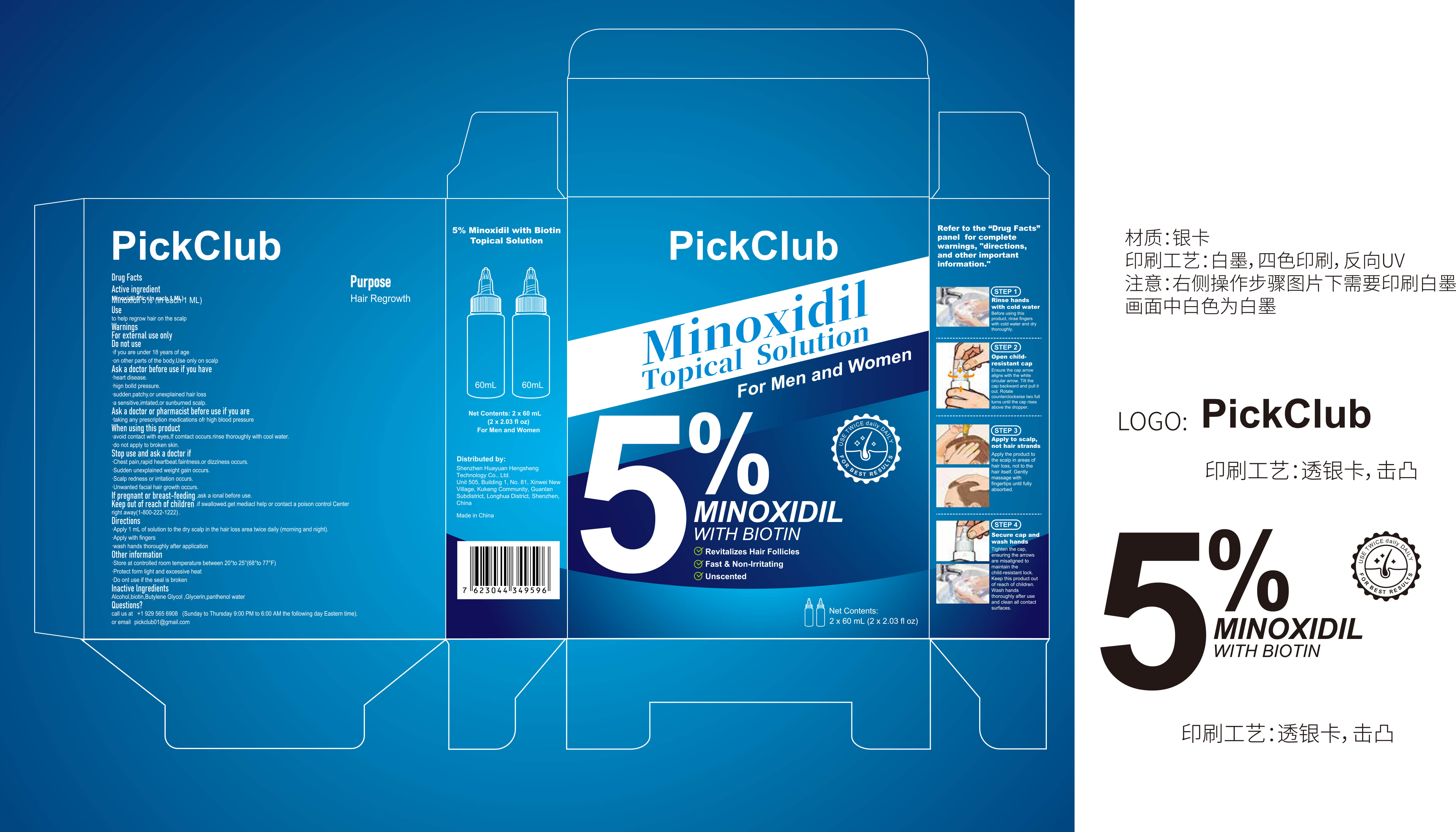 DRUG LABEL: 5% MINOXIDIL HAIR REGROWTH SERUM With Biotin
NDC: 87394-001 | Form: LIQUID
Manufacturer: Shenzhen Huayuan Hengsheng Technology Co., Ltd.
Category: otc | Type: HUMAN OTC DRUG LABEL
Date: 20260202

ACTIVE INGREDIENTS: MINOXIDIL 0.05 g/1 mL
INACTIVE INGREDIENTS: ALCOHOL; BIOTIN; WATER; BUTYLENE GLYCOL; GLYCERIN

87394-001 5% MINOXIDIL HAIR REGROWTH SERUM With Biotin

ACTIVE INGREDIENT

Minoxidil 5%

PURPOSE

Hair Regrowth

INDICATIONS AND USAGE

to help regrow hair on the scalp

WARNINGS

For external use only

DO NOT USE

if you are under 18 years of age
on other parts of the body,Use only on scalp

Ask a doctor before use if you have
heart disease.
hign bolld pressure.
sudden.patchy.or unexplained hair loss
a sensitive,imtated,or sunburned scalp.
Ask a doctor or pharmacist before use if you are
taking any prescription medications ofr high blood pressure
When using this product
avoid contact with eyes,lf comtact occurs.rinse thoroughly with cool water.
do not apply to broken skin.

STOP USE

Chest pain,rapid heartbeat.faintness.or dizziness occurs.
Sudden unexplained weight gain occurs.
Scalp redness or irritation occurs.
Unwanted facial hair growth occurs.

KEEP OUT OF REACH OF CHILDREN

if swallowed.get mediacl help or contact a poison control Center right away(1-800-222-1222)

DOSAGE AND ADMINISTRATION

Apply 1 mL of solution to the dry scalp in the hair loss area twice daily (morning and night).
Apply with fingers
wash hands thoroughly after application

INACTIVE INGREDIENT

Alcohol,biotin,Butylene Glycol ,Glycerin,panthenol water